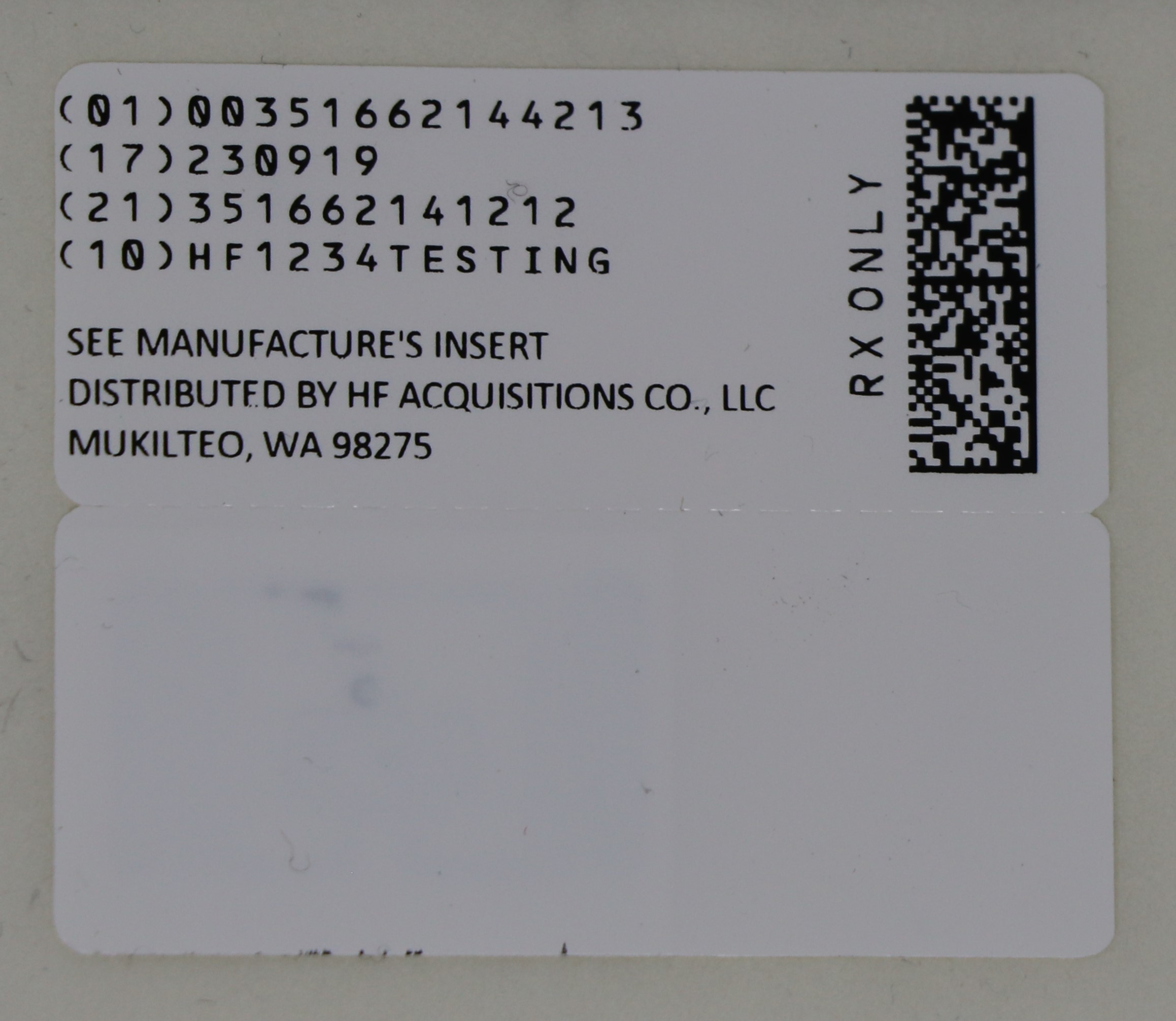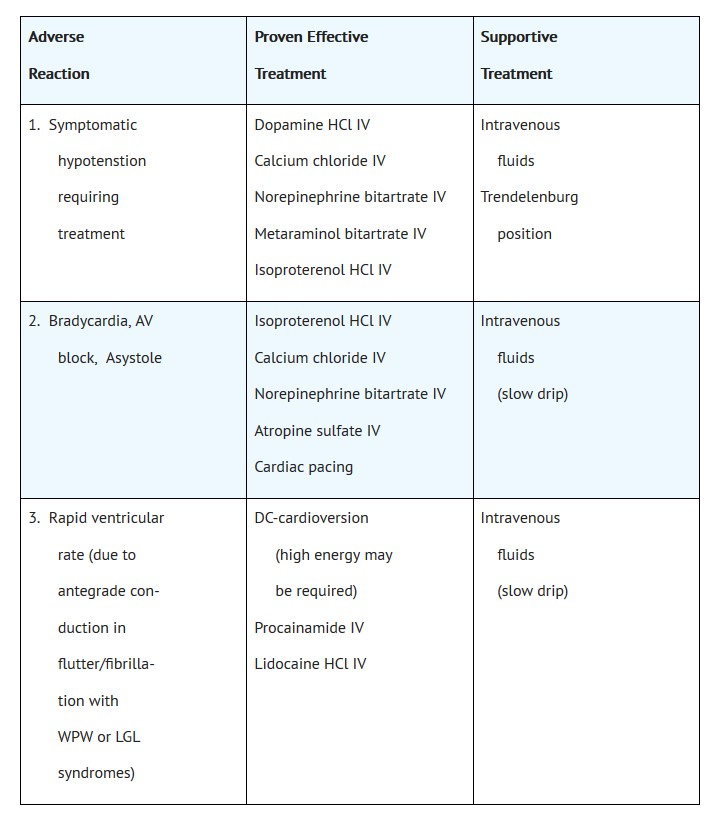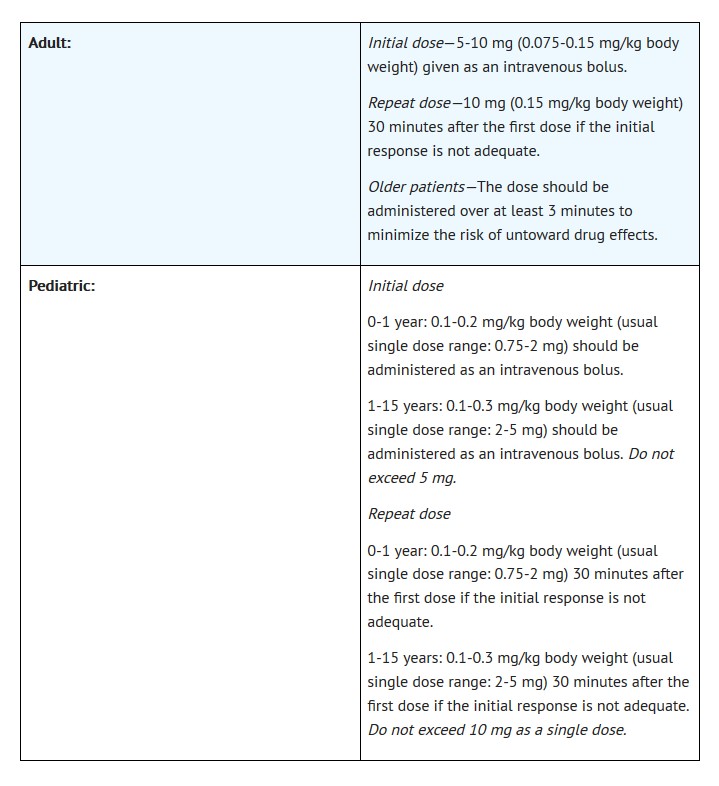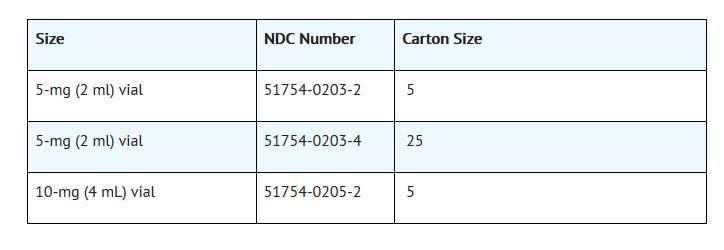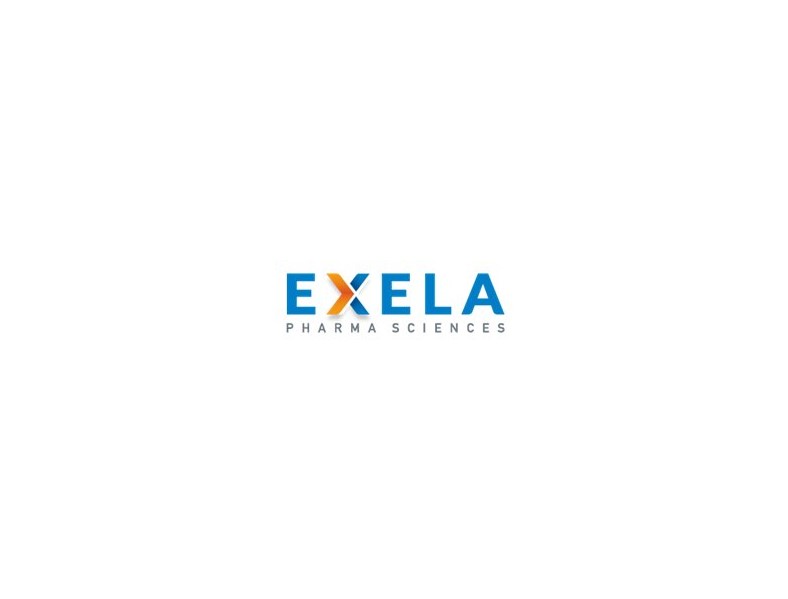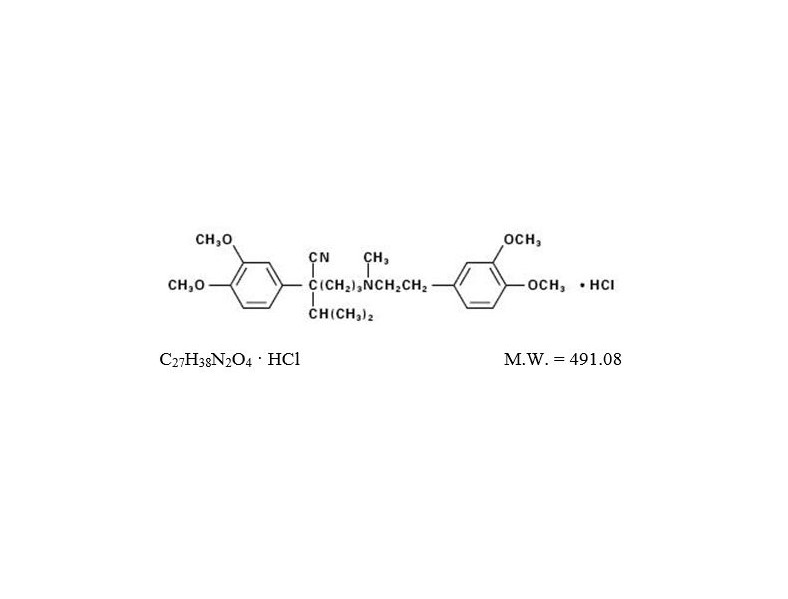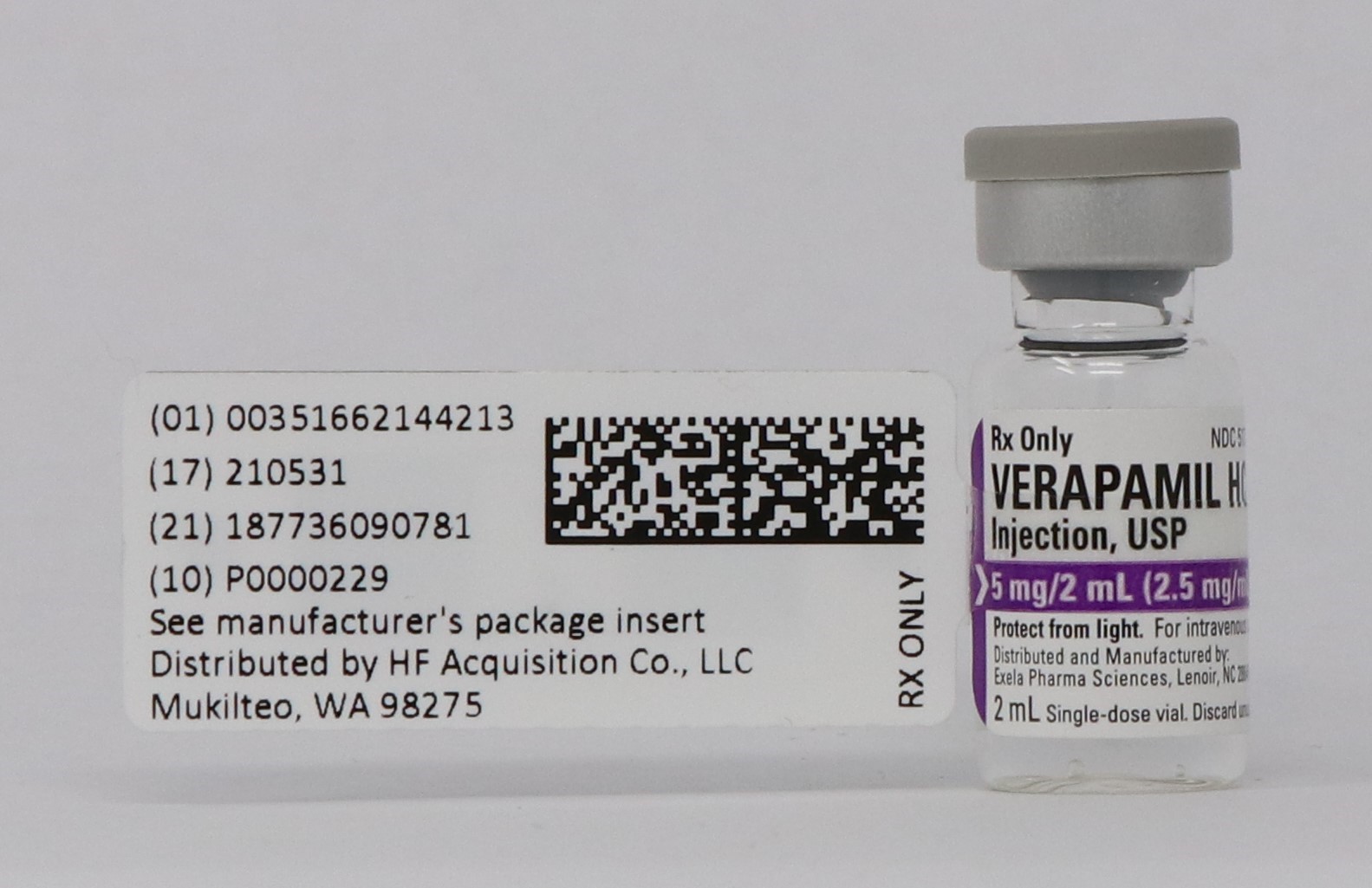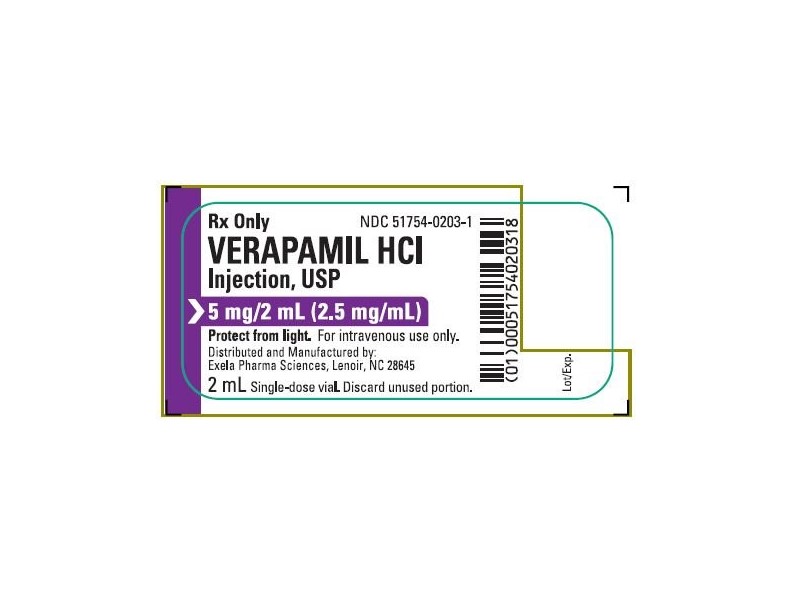 DRUG LABEL: VERAPAMIL HCI
NDC: 51662-1442 | Form: INJECTION
Manufacturer: HF Acquisition Co LLC, DBA HealthFirst
Category: prescription | Type: HUMAN PRESCRIPTION DRUG LABEL
Date: 20240226

ACTIVE INGREDIENTS: VERAPAMIL HYDROCHLORIDE 2.5 mg/1 mL
INACTIVE INGREDIENTS: SODIUM CHLORIDE 8.5 mg/1 mL; SODIUM HYDROXIDE; HYDROCHLORIC ACID

VERAPAMIL HCI INJECTION, USP 5mg/2mL (2.5mg/mL) 2mL VIAL

DESCRIPTION

Verapamil hydrochloride is a calcium antagonist or slow-channel inhibitor available as a sterile solution for intravenous injection in 5-mg (2 ml) and 10-mg (4 ml) vials. Each form contains Verapamil HCl 2.5 mg/ml and sodium chloride 8.5 mg/ml in water for injection. Hydrochloric acid and/or sodium hydroxide is used for pH adjustment. The pH of the solution is between 4.1 and 6.0.

The structural formula of verapamil HCl is given below:

Benzeneacetonitrile, α-[3-[[2-(3,4-dimethoxyphenyl)ethyl] methylamino]propyl]-3,4-dimethoxy-α-(1-methylethyl) hydrochloride

Verapamil hydrochloride is an almost white, crystalline powder, practically free of odor, with a bitter taste. It is soluble in water, chloroform, and methanol. Verapamil hydrochloride is not chemically related to other antiarrhythmic drugs.

CLINICAL PHARMACOLOGY

Mechanism of action: Verapamil inhibits the calcium ion (and possibly sodium ion) influx through slow channels into conductile and contractile myocardial cells and vascular smooth muscle cells. The antiarrhythmic effect of Verapamil appears to be due to its effect on the slow channel in cells of the cardiac conductile system.

Electrical activity through the SA and AV nodes depends, to a significant degree, upon calcium influx through the slow channel. By inhibiting this influx, Verapamil slows AV conduction and prolongs the effective refractory period within the AV node in a rate-related manner. This effect results in a reduction of the ventricular rate in patients with atrial flutter and/or atrial fibrillation and a rapid ventricular response. By interrupting reentry at the AV node, Verapamil can restore normal sinus rhythm in patients with paroxysmal supraventricular tachycardias (PSVT), including Wolff-Parkinson-White (WPW) syndrome. Verapamil has no effect on conduction across accessory bypass tracts. Verapamil does not alter the normal atrial action potential or intraventricular conduction time but depresses amplitude, velocity of depolarization, and conduction in depressed atrial fibers.

In the isolated rabbit heart, concentrations of Verapamil that markedly affect SA nodal fibers or fibers in the upper and middle regions of the AV node have very little effect on fibers in the lower AV node (NH region) and no effect on atrial action potentials or His bundle fibers.

Verapamil does not induce peripheral arterial spasm.

Verapamil has a local anesthetic action that is 1.6 times that of procaine on an equimolar basis. It is not known whether this action is important at the doses used in man.

Verapamil does not alter total serum calcium levels.

Hemodynamics: Verapamil reduces afterload and myocardial contractility. In most patients, including those with organic cardiac disease, the negative inotropic action of Verapamil is countered by reduction of afterload, and cardiac index is usually not reduced, but in patients with moderately severe to severe cardiac dysfunction (pulmonary wedge pressure above 20 mm Hg, ejection fraction less than 30%), acute worsening of heart failure may be seen. Peak therapeutic effects occur within 3 to 5 minutes after a bolus injection. The commonly used intravenous doses of 5-10 mg Verapamil produce transient, usually asymptomatic, reduction in normal systemic arterial pressure, systemic vascular resistance and contractility; left ventricular filling pressure is slightly increased.

Pharmacokinetics: Intravenously administered Verapamil has been shown to be rapidly metabolized. Following intravenous infusion in man, verapamil is eliminated bi-exponentially, with a rapid early distribution phase (half-life about 4 minutes) and a slower terminal elimination phase (half-life 2-5 hours). In healthy men, orally administered Verapamil undergoes extensive metabolism in the liver, with 12 metabolites having been identified, most in only trace amounts. The major metabolites have been identified as various N- and O-dealkylated products of Verapamil. Approximately 70% of an administered dose is excreted in the urine and 16% or more in the feces within 5 days. About 3% to 4% is excreted as unchanged drug.

INDICATIONS & USAGE

Verapamil is indicated for the treatment of supraventricular tachyarrhythmias, including:

•
Rapid conversion to sinus rhythm of paroxysmal supraventricular tachycardias, including those associated with accessory bypass tracts (Wolff-Parkinson-White [WPW] and Lown-Ganong-Levine [LGL] syndromes). When clinically advisable, appropriate vagal maneuvers (e.g., Valsalva maneuver) should be attempted prior to Verapamil administration.
•
Temporary control of rapid ventricular rate in atrial flutter or atrial fibrillation, except when the atrial flutter and/or atrial fibrillation are associated with accessory bypass tracts (Wolff-Parkinson-White [WPW] and Lown-Ganong-Levine [LGL] syndromes).

In controlled studies in the U.S., about 60% of patients with supraventricular tachycardia converted to normal sinus rhythm within 10 minutes after intravenous Verapamil hydrochloride. Uncontrolled studies reported in the world literature describe a conversion rate of about 80%. About 70% of patients with atrial flutter and/or fibrillation with a fast ventricular rate respond with a decrease in heart rate of at least 20%. Conversion of atrial flutter or fibrillation to sinus rhythm is uncommon (about 10%) after Verapamil hydrochloride and may reflect the spontaneous conversion rate, since the conversion rate after placebo was similar. The effect of a single injection lasts for 30–60 minutes when conversion to sinus rhythm does not occur.

Because a small fraction (<1.0%) of patients treated with Verapamil hydrochloride respond with life-threatening adverse responses (rapid ventricular rate in atrial flutter/fibrillation with an accessory bypass tract, marked hypotension, or extreme bradycardia/asystole—see Contraindications and Warnings), the initial use of intravenous Verapamil hydrochloride should, if possible, be in a treatment setting with monitoring and resuscitation facilities, including DC-cardioversion capability (see Suggested Treatment of Acute Cardiovascular Adverse Reactions). As familiarity with the patient’s response is gained, an office setting may be acceptable.

Cardioversion has been used safely and effectively after intravenous Verapamil.

CONTRAINDICATIONS

Verapamil hydrochloride injection is contraindicated in:

1.
Severe hypotension or cardiogenic shock
2.
Second- or third-degree AV block (except in patients with a functioning artificial ventricular pacemaker)
3.
Sick sinus syndrome (except in patients with a functioning artificial ventricular pacemaker)
4.
Severe congestive heart failure (unless secondary to a supraventricular tachycardia amenable to Verapamil therapy)
5.
Patients receiving intravenous beta-adrenergic blocking drugs (e.g., propranolol). Intravenous Verapamil and intravenous beta-adrenergic blocking drugs should not be administered in close proximity to each other (within a few hours), since both may have a depressant effect on myocardial contractility and AV conduction.
6.
Patients with atrial flutter or atrial fibrillation and an accessory bypass tract (e.g., Wolff-Parkinson-White, Lown-Ganong-Levine syndromes). These patients are at risk to develop ventricular tachyarrhythmia including ventricular fibrillation if Verapamil is administered.
7.
Ventricular tachycardia. Administration of intravenous Verapamil to patients with wide-complex ventricular tachycardia (QRS≥ 0.12 sec) can result in marked hemodynamic deterioration and ventricular fibrillation. Proper pretherapy diagnosis and differentiation from wide-complex supraventricular tachycardia is imperative in the emergency room setting.
8.
Known hypersensitivity to Verapamil hydrochloride

WARNINGS

VERAPAMIL SHOULD BE GIVEN AS A SLOW INTRAVENOUS INJECTION OVER AT LEAST A TWO-MINUTE PERIOD OF TIME. (See Dosage and Administration.)

Hypotension: Intravenous Verapamil often produces a decrease in blood pressure below baseline levels that is usually transient and asymptomatic but may result in dizziness. Systolic pressure less than 90 mm Hg and/or diastolic pressure less than 60 mm Hg was seen in 5%-10% of patients in controlled U.S. trials in supraventricular tachycardia and in about 10% of the patients with atrial flutter/fibrillation. The incidence of symptomatic hypotension observed in studies conducted in the U.S. was approximately 1.5%. Three of the five symptomatic patients required pharmacologic treatment (norepinephrine bitartrate IV, metaraminol bitartrate IV, or 10% calcium gluconate IV). All recovered without sequelae.

Extreme bradycardia/asystole: Verapamil affects the AV and SA nodes and rarely may produce second- or third-degree AV block, bradycardia, and, in extreme cases, asystole. This is more likely to occur in patients with a sick sinus syndrome (SA nodal disease), which is more common in older patients. Bradycardia associated with sick sinus syndrome was reported in 0.3% of the patients treated in controlled double-blind trials in the U.S. The total incidence of bradycardia (ventricular rate less than 60 beats/min) was 1.2% in these studies. Asystole in patients other than those with sick sinus syndrome is usually of short duration (few seconds or less), with spontaneous return to AV nodal or normal sinus rhythm. If this does not occur promptly, appropriate treatment should be initiated immediately. (See Adverse Reactions including suggested treatment of adverse reactions.)

Heart failure: When heart failure is not severe or rate related, it should be controlled with digitalis glycosides and diuretics, as appropriate, before Verapamil is used.

In patients with moderately severe to severe cardiac dysfunction (pulmonary wedge pressure above 20 mm Hg, ejection fraction less than 30%), acute worsening of heart failure may be seen.

Concomitant antiarrhythmic therapy:

Digitalis: Intravenous Verapamil has been used concomitantly with digitalis preparations without the occurrence of serious adverse effects. However, since both drugs slow AV conduction, patients should be monitored for AV block or excessive bradycardia.

Procainamide: Intravenous Verapamil has been administered to a small number of patients receiving oral procainamide without the occurrence of serious adverse effects.

Quinidine: Intravenous Verapamil has been administered to a small number of patients receiving oral quinidine without the occurrence of serious adverse effects. However a few cases of hypotension have been reported in patients taking oral quinidine who received intravenous Verapamil. Caution should therefore be used when employing this combination of drugs.

Beta-adrenergic blocking drugs: Intravenous Verapamil has been administered to patients receiving oral beta blockers without the development of serious adverse effects. However, since both drugs may depress myocardial contractility or AV conduction, the possibility of detrimental interactions should be considered. The concomitant administration of intravenous beta blockers and intravenous Verapamil has resulted in serious adverse reactions (see Contraindications), especially in patients with severe cardiomyopathy, congestive heart failure, or recent myocardial infarction.

Disopyramide: Until data on possible interactions between Verapamil and disopyramide are obtained, disopyramide should not be administered within 48 hours before or 24 hours after Verapamil administration.

Heart block: Verapamil prolongs AV conduction time. While high-degree AV block has not been observed in controlled clinical trials in the U.S., a low percentage (less than 0.5%) has been reported in the world literature. Development of second- or third-degree AV block or unifascicular, bifascicular, or trifascicular bundle branch block requires reduction in subsequent doses or discontinuation of Verapamil and institution of appropriate therapy, if needed. (See Adverse Reactions and Concomitant antiarrhythmic therapy.)

Hepatic and renal failure: Significant hepatic and renal failure should not increase the effects of a single intravenous dose of Verapamil but may prolong its duration. Repeated injections of intravenous Verapamil in such patients may lead to accumulation and an excessive pharmacologic effect of the drug. There is no experience to guide use of multiple doses in such patients, and this generally should be avoided. If repeated injections are essential, blood pressure and PR interval should be closely monitored and smaller repeat doses should be utilized. Data on the clearance of Verapamil by dialysis are not yet available.

Premature ventricular contractions: During conversion to normal sinus rhythm or marked reduction in ventricular rate, a few benign complexes of unusual appearance (sometimes resembling premature ventricular contractions) may be seen after treatment with Verapamil. Similar complexes are seen during spontaneous conversion of supraventricular tachycardia and after DC-cardioversion or other pharmacologic therapy. These complexes appear to have no clinical significance.

Duchenne’s muscular dystrophy: Intravenous Verapamil can precipitate respiratory muscle failure in these patients and should, therefore, be used with caution.

Increased intracranial pressure: Intravenous Verapamil has been seen to increase intracranial pressure in patients with supratentorial tumors at the time of anesthesia induction. Caution should be taken and appropriate monitoring performed.

PRECAUTIONS

Drug interactions: (See Warnings: Concomitant antiarrhythmic therapy.) Intravenous Verapamil has been used concomitantly with other cardioactive drugs (e.g., digitalis) without evidence of serious negative drug interactions. In rare instances, including when patients with severe cardiomyopathy, congestive heart failure, or recent myocardial infarction were given intravenous beta-adrenergic blocking agents or disopyramide concomitantly with intravenous Verapamil, serious adverse effects have occurred. Concomitant use of Verapamil with agents that decrease adrenergic function may result in an exaggerated hypotensive response. Animal studies suggest concomitant use of intravenous Verapamil and intravenous dantrolene sodium may result in cardiovascular collapse. The clinical relevance of these findings is unknown.

Cimetidine has no effect on intravenous Verapamil kinetics. As Verapamil is highly bound to plasma proteins, it should be administered with caution to patients receiving other highly protein-bound drugs.

Animal experiments have shown that inhalation anesthetics depress cardiovascular activity by decreasing the inward movement of calcium ions. When used concomitantly, inhalation anesthetics and calcium antagonists, such as Verapamil, should each be titrated carefully to avoid excessive cardiovascular depression.

Clinical data and animal studies suggest that Verapamil may potentiate the activity of neuromuscular blocking agents (curare-like and depolarizing). It may be necessary to decrease the dose of Verapamil and/or the dose of the neuromuscular blocking agent when the drugs are used concomitantly.

Telithromycin:Hypotension and bradyarrhythmias have been observed in patients receiving concurrent telithromycin, an antibiotic in the ketolide class.

Clonidine: Sinus bradycardia resulting in hospitalization and pacemaker insertion has been reported in association with the use of clonidine concurrently with Verapamil. Monitor heart rate in patients receiving concomitant Verapamil and clonidine.

HMG-CoA reductase inhibitors: The use of HMG-CoA reductase inhibitors that are CYP3A4 substrates in combination with Verapamil has been associated with reports of myopathy/rhabdomyolysis.

Co-administration of multiple doses of 10 mg of Verapamil with 80 mg simvastatin resulted in exposure to simvastatin 2.5-fold that following simvastatin alone. Limit the dose of simvastatin in patients on Verapamil to 10 mg daily. Limit the daily dose of lovastatin to 40 mg. Lower starting and maintenance doses of other CYP3A4 substrates (e.g., atorvastatin) may be required as Verapamil may increase the plasma concentration of these drugs.

Ivabradine: Concurrent use of verapamil increases exposure to Ivabradine and may exacerbate bradycardia and conductions disturbances. Avoid concomitant use of Ivabradine and verapamil.

Pregnancy: Pregnancy Category C. Reproduction studies have been performed in rabbits and rats at oral Verapamil doses up to 1.5 (15 mg/kg/day) and 6 (60 mg/kg/day) times the human oral daily dose, respectively, and have revealed no evidence of teratogenicity. In the rat, however, this multiple of the human dose was embryocidal and retarded fetal growth and development, probably because of adverse maternal effects reflected in reduced weight gains of the dams. This oral dose has also been shown to cause hypotension in rats. There are, however, no adequate and well-controlled studies in pregnant women. Because animal reproduction studies are not always predictive of human response, this drug should be used during pregnancy only if clearly needed.

Labor and delivery: There have been few controlled studies to determine whether the use of Verapamil during labor or delivery has immediate or delayed adverse effects on the fetus, or whether it prolongs the duration of labor or increases the need for forceps delivery or other obstetric intervention. Such adverse experiences have not been reported in the literature, despite a long history of use of intravenous Verapamil in Europe in the treatment of cardiac side effects of beta-adrenergic agonist agents used to treat premature labor.

Nursing mothers: Verapamil crosses the placental barrier and can be detected in umbilical vein blood at delivery. Also, verapamil is excreted in human milk. Because of the potential for serious adverse reactions in nursing infants from Verapamil, nursing should be discontinued while Verapamil is administered.

Pediatric use: Controlled studies with Verapamil have not been conducted in pediatric patients, but uncontrolled experience with intravenous administration in more than 250 patients, about half under 12 months of age and about 25% newborn, indicates that results of treatment are similar to those in adults. However, in rare instances, severe hemodynamic side effects have occurred following the intravenous administration of verapamil in neonates and infants. Caution should therefore be used when administering Verapamil to this group of pediatric patients. The most commonly used single doses in patients up to 12 months of age have ranged from 0.1 to 0.2 mg/kg of body weight, while in patients aged 1 to 15 years, the most commonly used single doses ranged from 0.1 to 0.3 mg/kg of body weight. Most of the patients received the lower dose of 0.1 mg/kg once, but in some cases, the dose was repeated once or twice every 10 to 30 minutes.

ADVERSE REACTIONS

The following reactions were reported with intravenous Verapamil use in controlled U.S. clinical trials involving 324 patients:

Cardiovascular: Symptomatic hypotension (1.5%); bradycardia (1.2%); severe tachycardia (1.0%). The worldwide experience in open clinical trials in more than 7,900 patients was similar.

Central nervous system effects: Dizziness (1.2%); headache (1.2%). Although rare, cases of seizures during verapamil injection has been reported.

Gastrointestinal: Nausea (0.9%); abdominal discomfort (0.6%).

In rare cases of hypersensitivity, broncho/laryngeal spasm accompanied by itch and urticaria has been reported.

The following reactions were reported in a few patients: emotional depression, rotary nystagmus, sleepiness, vertigo, muscle fatigue, or diaphoresis.

Suggested Treatment of Acute Cardiovascular Adverse Reactions*
The frequency of these adverse reactions was quite low, and experience with their treatment has been limited.

*Actual treatment and dosage should depend on the severity of the clinical situation and the judgment and experience of the treating physician.

OVERDOSAGE

Treatment of overdosage should be supportive and individualized. Beta-adrenergic stimulation and/or parenteral administration of calcium solutions (calcium chloride) have been effectively used in treatment of deliberate overdosage with oral Verapamil. Clinically significant hypotensive reactions or high-degree AV block should be treated with vasopressor agents or cardiac pacing, respectively. Asystole should be handled by the usual measures including isoproterenol hydrochloride, other vasopressor agents, or cardiopulmonary resuscitation (see ADVERSE REACTIONS-Suggested Treatment of Acute Cardiovascular Adverse Reactions).

DOSAGE & ADMINISTRATION

For intravenous use only. VERAPAMIL SHOULD BE GIVEN AS A SLOW INTRAVENOUS INJECTION OVER AT LEAST A TWO-MINUTE PERIOD OF TIME UNDER CONTINUOUS ECG AND BLOOD PRESSURE MONITORING. The recommended intravenous doses of Verapamil are as follows:

Note: Parenteral drug products should be inspected visually for particulate matter and discoloration prior to administration, whenever solution and container permit. Use only if solution is clear and vial seal is intact. Unused amount of solution should be discarded immediately following withdrawal of any portion of contents.

For stability reasons this product is not recommended for dilution with Sodium Lactate Injection USP in polyvinyl chloride bags. Admixing intravenous Verapamil with albumin, amphotericin B, hydralazine HCl, and trimethoprim with sulfamethoxazole should be avoided. Verapamil will precipitate in any solution with a pH above 6.0.

HOW SUPPLIED

VERAPAMIL HCI INJECTION, USP is supplied in the following dosage forms.
NDC 51662-1442-1
VERAPAMIL HCI INJECTION, USP 5mg/2mL (2.5mg/mL) 2mL VIAL

HF Acquisition Co LLC, DBA HealthFirst
Mukilteo, WA 98275

Also supplied in the following manufacture supplied dosage forms

All forms are individually packaged.

Store at 59° to 86°F (15° to 30°C) [See USP Controlled Room Temperature.]

SPL UNCLASSIFIED

Distributed and Manufactured By:
Exela Pharma Sciences

Lenoir, NC 28645

Revised May 2018